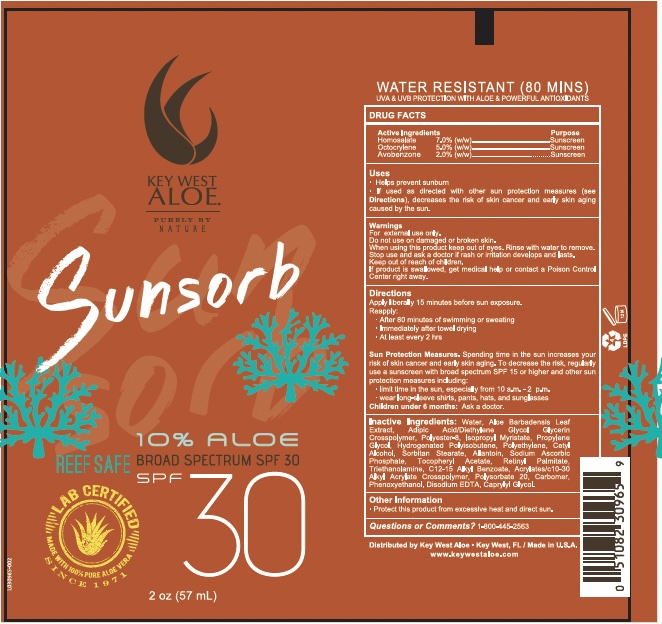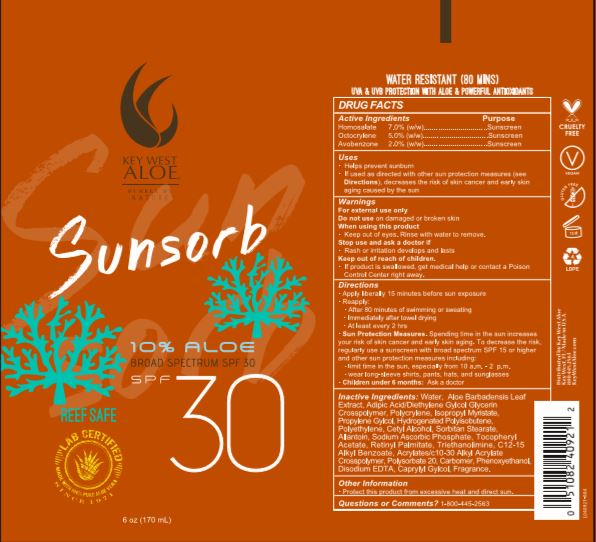 DRUG LABEL: Sunsorb Reef Safe SPF30
NDC: 65008-006 | Form: LOTION
Manufacturer: QS Key West Aloe, LLC
Category: otc | Type: HUMAN OTC DRUG LABEL
Date: 20251111

ACTIVE INGREDIENTS: HOMOSALATE 70 mg/1 g; OCTOCRYLENE 50 mg/1 g; AVOBENZONE 20 mg/1 g
INACTIVE INGREDIENTS: WATER; ALOE VERA LEAF; ADIPIC ACID/DIGLYCOL CROSSPOLYMER (20000 MPA.S); POLYESTER-8 (1400 MW, CYANODIPHENYLPROPENOYL CAPPED); ISOPROPYL MYRISTATE; PROPYLENE GLYCOL; HYDROGENATED POLYBUTENE (1300 MW); HIGH DENSITY POLYETHYLENE; CETYL ALCOHOL; SORBITAN MONOSTEARATE; ALLANTOIN; SODIUM ASCORBYL PHOSPHATE; .ALPHA.-TOCOPHEROL ACETATE, DL-; VITAMIN A PALMITATE; TROLAMINE; ALKYL (C12-15) BENZOATE; POLYSORBATE 20; CAPRYLYL GLYCOL; CARBOMER 940; PHENOXYETHANOL; EDETATE DISODIUM

SunsorbReef Safe SPF30

Active Ingredients

Homosalate 7.0% w/w

Octocrylene 5.0% w/w

Avobenzone 2.0% w/w

Purpose

Sunscreen

Uses

- Helps prevent sunburn

- If used as directed with other sun protection measures (see Directions), decreases the risk of skin cancer and early skin aging caused by the sun

Warnings

For external use only

Do not useon damaged or broken skin

When using this product

- Keep out of eyes. Rinse with water to remove.

Stop use and ask a doctor if

- Rash or irritation develops and lasts

Keep out of reach of children.

- If product is swallowed, get medical help or contact a Poison Control Center right away.

Directions

- Apply liberally 15 minutes before sun exposure

- Reapply

- After 80 minutes of swimming or sweating

- Immediately after towel drying

- At least every 2 hrs

- Sun Protection Measures. Spending time in the sun increases your risk of skin cancer and early skin aging. To decrease the risk, regularly use a sunscreen with broad spectrum SPF 15 or higher and other skin protection measures including:

- limit time in the sun, especially from 10 a.m. - 2 p.m.

- wear long-sleeve shirts, pants, hats, and sunglasses

- Children under 6 months: Ask a doctor

Inactive Ingredients:

Water, Aloe Barbadensis Leaf Extract, Adipic Acid/Diethylene Glycol Glycerin Crosspolymer, Polycrylene, Isopropyl Myristate, Propylene Glycol, Hydrogenated Polyisobutene, Polyethylene, Cetyl Alcohol, Sorbitan Stearate, Allantoin, Sodium Ascorbic Phosphate, Tocopheryl Acetate, Retinyl Palmitate, Triethanolamine, C12-15 Alkyl Benzoate, Acrylates/c10-30 Alkyl Acrylate Crosspolymer, Polysorbate 20, Carbomer, Phenoxyethanol, Disodium EDTA, Fragrance

Other Information

- Protect this product from excessive heat and direct sun.

Questions or Comments?

1-800-445-2563